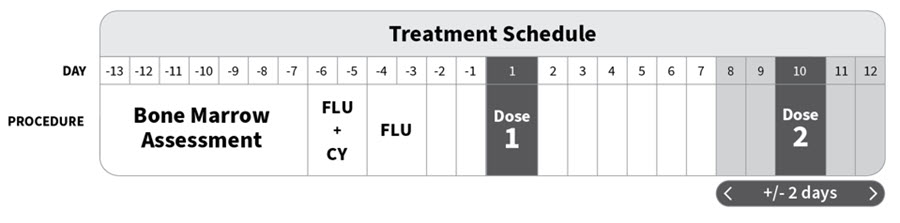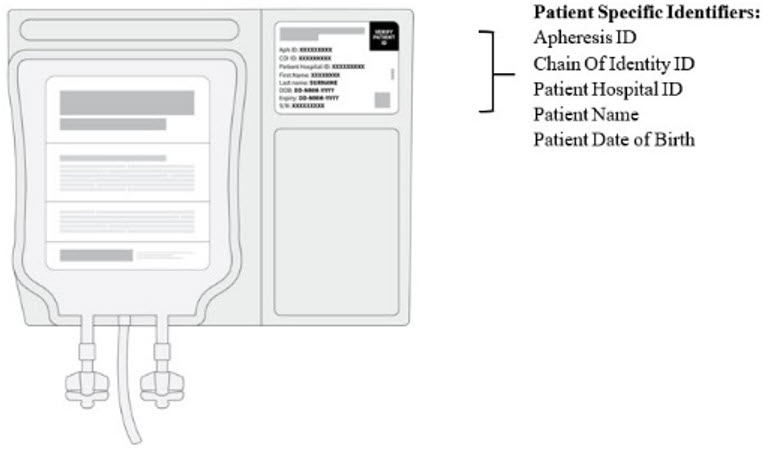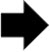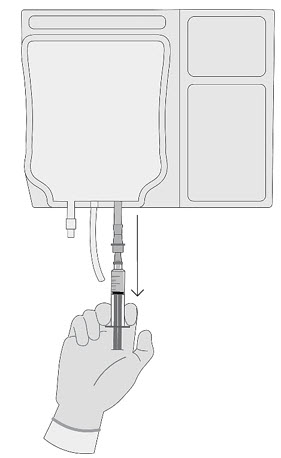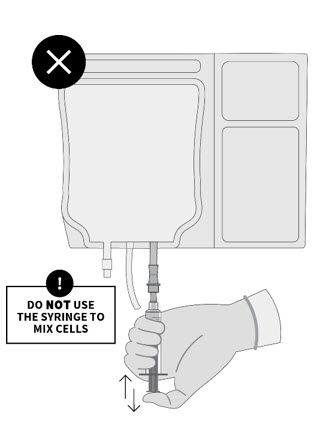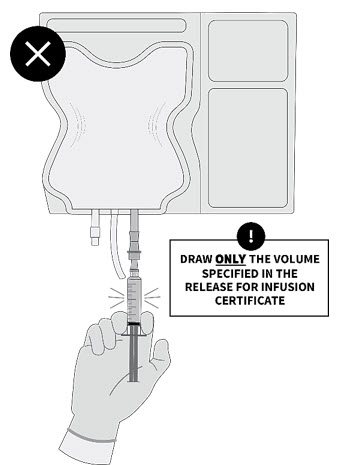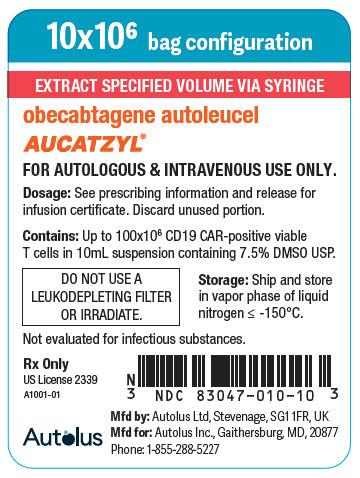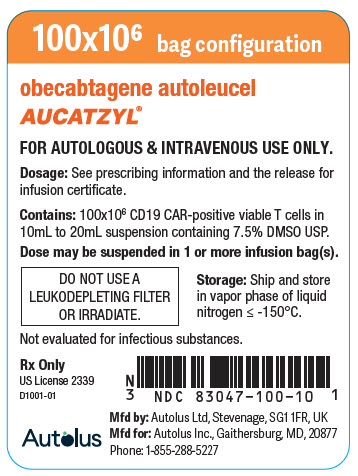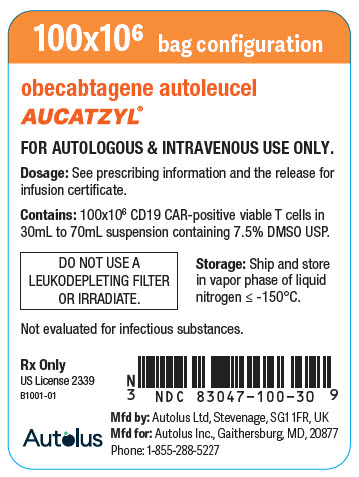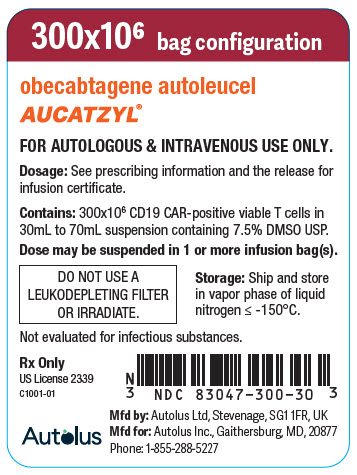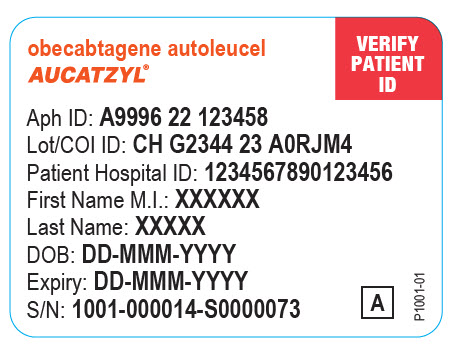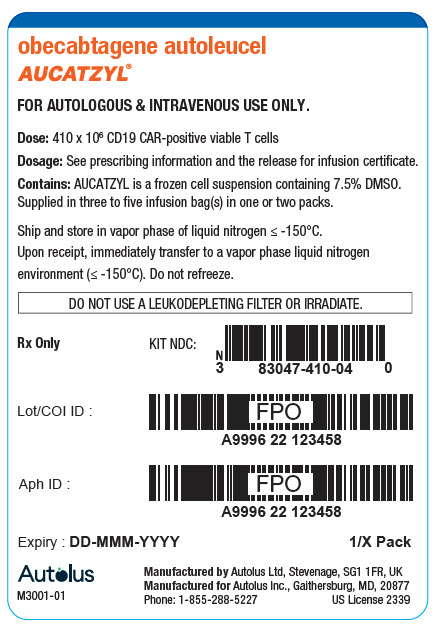 DRUG LABEL: AUCATZYL
NDC: 83047-410 | Form: KIT | Route: INTRAVENOUS
Manufacturer: Autolus Inc.
Category: other | Type: CELLULAR THERAPY
Date: 20250818

ACTIVE INGREDIENTS: Obecabtagene autoleucel 10000000 1/1 1; Obecabtagene autoleucel 100000000 1/1 1; Obecabtagene autoleucel 300000000 1/1 1

HIGHLIGHTS OF PRESCRIBING INFORMATION

These highlights do not include all the information needed to use AUCATZYL safely and effectively. See full prescribing information for AUCATZYL.
AUCATZYL® (obecabtagene autoleucel) suspension for intravenous infusion
Initial U.S. Approval: 2024

WARNING: CYTOKINE RELEASE SYNDROME, NEUROLOGIC TOXICITIES, and SECONDARY HEMATOLOGICAL MALIGNANCIES

See full prescribing information for complete boxed warning.

Cytokine Release Syndrome (CRS) occurred in patients receiving AUCATZYL. Do not administer AUCATZYL to patients with active infection or inflammatory disorders. Prior to administering AUCATZYL, ensure that healthcare providers have immediate access to medications and resuscitative equipment to manage CRS. (2.2, 2.3, 5.1).

Immune Effector Cell-Associated Neurotoxicity Syndrome (ICANS), including fatal or life-threatening reactions, occurred in patients receiving AUCATZYL, including concurrently with CRS or after CRS resolution. Monitor for neurologic signs and symptoms after treatment with AUCATZYL. Prior to administering AUCATZYL, ensure that healthcare providers have immediate access to medications and resuscitative equipment to manage neurologic toxicities (2.2, 2.3, 5.2).

T cell malignancies have occurred following treatment of hematologic malignancies with BCMA- and CD19-directed genetically modified autologous T cell immunotherapies (5.8).

RECENT MAJOR CHANGES

Dosage and Administration (2.4) | 08/2025
Warnings and Precautions (5.1, 5.2) | 08/2025
Warnings and Precautions, Effects on Ability to Drive and Use Machines (5.2) | Removed 08/2025

1 INDICATION AND USAGE

AUCATZYL is a CD19-directed genetically modified autologous T cell immunotherapy indicated for the treatment of adults with relapsed or refractory B-cell precursor acute lymphoblastic leukemia (ALL) (1).

2 DOSAGE AND ADMINISTRATION

For autologous use only. For intravenous use only.

Do NOT use a leukodepleting filter (2.4).

Prior to infusion

- Administer a lymphodepleting chemotherapy regimen of fludarabine/cyclophosphamide. (2.3).
- Ensure availability of bone marrow assessment results from a sample obtained within 7 days prior to start of lymphodepleting chemotherapy (2.3).
- Premedicate with acetaminophen (2.3).
- Confirm availability of tocilizumab prior to infusion (2.3).

AUCATZYL Dose and Administration

- Verify patient's identity prior to infusion (2.3).
- Dosing is based on the Dose Schedule Planner (2.3).
- The total recommended dose of AUCATZYL is 410 × 10^6 CD19 chimeric antigen receptor (CAR)-positive viable T cells (2.1).
- The treatment regimen consists of a split dose infusion to be administered on Day 1 and Day 10 (± 2 days) (2.1). Dose to be administered is determined by the patient bone marrow blast assessment.
- See Full Prescribing Information for important preparation and administration information (2.3, 2.4).

3 DOSAGE FORMS AND STRENGTHS

- AUCATZYL is a cell suspension for infusion (3).
- AUCATZYL contains a total recommended dose of 410 × 10^6 CD19 CAR-positive viable T cells supplied in 3 to 5 infusion bags (3).

4 CONTRAINDICATIONS

None (4).

5 WARNINGS AND PRECAUTIONS

- Prolonged Cytopenias: Patients may exhibit Grade 3 or higher cytopenias for several weeks following AUCATZYL infusion. Monitor complete blood counts (5.3).
- Infections: Monitor patients for signs and symptoms of infection; treat appropriately (5.4).
- Hypogammaglobulinemia: Monitor and consider immunoglobulin replacement therapy (5.5).
- Hemophagocytic Lymphohistiocytosis/ Macrophage Activation Syndrome: Administer treatment per institutional standards (5.6).
- Hypersensitivity Reactions: Monitor for hypersensitivity reactions during infusion (5.7).
- Secondary Malignancies: T cell malignancies have occurred following treatment of hematologic malignancies with BCMA- and CD19-directed genetically modified autologous T cell immunotherapies. In the event that a secondary malignancy occurs after treatment with AUCATZYL, contact Autolus Inc at 1-855-288-5227 (5.8).

6 ADVERSE REACTIONS

The most common (non-laboratory) adverse reactions (incidence ≥ 20%) are: CRS, infections - pathogen unspecified, musculoskeletal pain, viral infections, fever, nausea, bacterial infectious disorders, diarrhea, febrile neutropenia, ICANS, hypotension, pain, fatigue, headache, encephalopathy, and hemorrhage (6.1).

To report SUSPECTED ADVERSE REACTIONS, contact Autolus Inc at toll-free phone 1-855-288-5227 or FDA at 1-800-FDA-1088 or www.fda.gov/medwatch (17).

FULL PRESCRIBING INFORMATION

WARNING: CYTOKINE RELEASE SYNDROME, NEUROLOGIC TOXICITIES, and SECONDARY HEMATOLOGICAL MALIGNANCIES

- Cytokine Release Syndrome (CRS) occurred in patients receiving AUCATZYL. Do not administer AUCATZYL to patients with active infection or inflammatory disorders. Prior to administering AUCATZYL, ensure that healthcare providers have immediate access to medications and resuscitative equipment to manage CRS [see Dosage and Administration (2.2, 2.3), Warnings and Precautions (5.1)].
- Immune Effector Cell-Associated Neurotoxicity Syndrome (ICANS), including fatal or life-threatening reactions, occurred in patients receiving AUCATZYL, including concurrently with CRS or after CRS resolution. Monitor for neurologic signs and symptoms after treatment with AUCATZYL. Prior to administering AUCATZYL, ensure that healthcare providers have immediate access to medications and resuscitative equipment to manage neurologic toxicities. Provide supportive care and/or corticosteroids, as needed [see Dosage and Administration (2.2, 2.3), Warnings and Precautions (5.2)].
- T cell malignancies have occurred following treatment of hematologic malignancies with BCMA- and CD19-directed genetically modified autologous T cell immunotherapies [see Warnings and Precautions (5.8)].

1 INDICATION AND USAGE

AUCATZYL is a CD19-directed genetically modified autologous T cell immunotherapy indicated for the treatment of adults with relapsed or refractory B-cell precursor acute lymphoblastic leukemia (ALL).

2 DOSAGE AND ADMINISTRATION

For autologous use only. For intravenous use only.

Strictly follow Administration instructions to minimize dosing errors [see Overdosage (10)].

2.1 Dose

The total recommended dose of AUCATZYL is 410 × 10^6 CD19 chimeric antigen receptor (CAR)-positive viable T cells supplied in three to five infusion bags. Bags are supplied in three color-coded bag configurations (10 × 10^6, 100 × 10^6, 300 × 10^6) for split dose administration.

Table 1: AUCATZYL Infusion Bag Configurations
CAR-positive T Cell Dose (Bag Configuration) | Color Code | Volume | Fully Infused
10 × 10^6 | Blue | 10 mL | No (See Section 2.3)
100 × 10^6 | Orange | Variable | Yes
300 × 10^6 | Red | Variable | Yes

The treatment regimen consists of a split dose infusion to be administered on Day 1 and Day 10 (± 2 days), see Figure 1 and Figure 3.

- The dosage regimen will be determined by the tumor burden assessed by bone marrow blast percentage from a sample obtained within 7 days prior to the start of lymphodepletion [see Dosing and Administration (2.3, 2.4), Figure 1 and Figure 3].
- See the Release for Infusion certificate and Dose Schedule Planner for the actual cell counts and volumes to be infused and to select the appropriate dosage regimen [see Dosage and Administration (2.4) and Dosage Forms and Strengths (3)].

2.2 Dosage Modification for Adverse Reactions

Table 2: Dosage Modifications Intended to Reduce the Risk of Adverse Reactions
Adverse Event | Severity [1. Based on the Common Terminology Criteria for Adverse Events (CTCAE) v5.0. Grade 1 is mild, Grade 2 is moderate, Grade 3 is severe, and Grade 4 is life-threatening.] | Actions Second Split Dose Day 10 (± 2 days)
Cytokine Release Syndrome following the first split dose [see Warnings and Precautions (5.1)]. | Grade 2 | Consider postponing AUCATZYL infusion up to Day 21 to allow for the CRS to resolve to Grade ≤ 1.
Cytokine Release Syndrome following the first split dose [see Warnings and Precautions (5.1)]. | Grade ≥ 3 | Discontinue treatment.
Immune Effector Cell-associated Neurotoxicity Syndrome following the first split dose [see Warnings and Precautions (5.2)]. | Grade 1 | Consider postponing AUCATZYL infusion up to Day 21 to allow for the ICANS to completely resolve.
Immune Effector Cell-associated Neurotoxicity Syndrome following the first split dose [see Warnings and Precautions (5.2)]. | Grade ≥ 2 | Discontinue treatment.
Pulmonary or cardiac toxicities following the first split dose. | Grade ≥ 3 | Discontinue treatment.
Severe intercurrent infection at the time of AUCATZYL infusion [see Warnings and Precautions (5.4)]. | Grade ≥ 3 | Consider postponing AUCATZYL infusion up to Day 21 until the severe intercurrent infection is considered controlled.
Requirement for supplementary oxygen. | Grade ≥ 3 | Consider postponing AUCATZYL treatment up to Day 21 to allow for the adverse reaction to resolve.
Other clinically relevant adverse reactions following the first split dose [see Warnings and Precautions (5)]. | Grade ≥ 3 | Consider postponing AUCATZYL infusion up to Day 21 to allow for the adverse reaction to resolve.

2.3 Administration

AUCATZYL is for autologous use only. The patient's identity must match the patient identifiers on the AUCATZYL infusion bag. Do not infuse AUCATZYL if the information on the patient-specific label does not match the intended patient.

Preparing the Patient for AUCATZYL Infusion

Bone marrow assessment

- A bone marrow assessment must be available from a sample obtained within 7 days prior to the commencement of the lymphodepleting chemotherapy treatment, see Figure 1.

Figure 1: AUCATZYL Treatment Schedule

- The bone marrow assessment will be used to determine the AUCATZYL dosage regimen based on a Bone Marrow Blast of > 20% or ≤ 20%, see Figure 3.
  - If the bone marrow assessment results are inconclusive:
    - Repeat biopsy or aspirate, NOTE a repeat biopsy or aspirate is only possible if lymphodepleting chemotherapy treatment has not started.
    - If results remain inconclusive, proceed with the Bone Marrow Blast of > 20% (i.e., administration of the 10 × 10^6 dose on Day 1) per the AUCATZYL Dose Schedule Planner.

Pretreatment

- Confirm availability of AUCATZYL prior to starting the lymphodepleting chemotherapy treatment.
- Administer the lymphodepleting chemotherapy regimen before infusion of AUCATZYL: fludarabine (FLU) 30 mg/m^2/day intravenously (IV) for four days and cyclophosphamide (CY) 500 mg/m^2/day IV for two days starting with the first dose of fludarabine. (total dose: FLU 120 mg/m^2; CY 1000 mg/m^2), see Figure 1. Infuse AUCATZYL 3 days (± 1 day) after completion of lymphodepleting chemotherapy treatment (Day 1), allowing a minimum 48-hour washout.
- Delay AUCATZYL treatment if the patient is experiencing severe intercurrent infection. If the patient requires supplementary oxygen AUCATZYL should only be infused if considered appropriate based on the treating physician's benefit/risk assessment.

A delay to the second split dose may be required to manage toxicities [see Dosage Modification for Adverse Reactions (2.2) and Warnings and Precautions (5)].

Premedication

- To minimize the risk of an infusion reaction, premedicate with acetaminophen approximately 30 minutes prior to AUCATZYL infusion.
- Avoid prophylactic use of systemic corticosteroids as they may interfere with the activity of AUCATZYL.

Receipt and storage of AUCATZYL

- AUCATZYL is supplied directly to the cellular therapy laboratory associated with the infusion center in the vapor phase of a liquid nitrogen shipper [see How Supplied/Storage and Handling (16)].
  Confirm the patient's identity on the infusion bags with the patient identifiers on the shipper, see Figure 2.

Figure 2: Patient Specific Identifiers

- Keep the infusion bag(s) in the metal cassette(s) and transfer AUCATZYL to the onsite controlled-access vapor phase of liquid nitrogen for storage below minus 150°C until ready for thaw and administration.
  - Time out of the vapor phase liquid nitrogen environment should be kept to an absolute minimum to avoid premature product thaw (recommend not to exceed 90 seconds).

Planning prior to AUCATZYL preparation

- The patient batch specific Release for Infusion certificate and Dose Schedule Planner will be provided in the shipper and via Autolus' Scheduling Portal.
- Confirm the patient identifiers on the Release for Infusion certificate and infusion bags match, see Figure 2.

1. Ensure the patient's bone marrow assessment results are available.
  NOTE: The patient's bone marrow assessment results will be used to select the appropriate dosing regimen based on a Bone Marrow Blast of > 20% or ≤ 20%, see Figure 3.
2. The AUCATZYL Dose Schedule Planner is provided with the Release for Infusion certificate and assists the determination of the appropriate dose regimen to be administered on Day 1 (3 days (± 1 day) after the completion of lymphodepleting chemotherapy) and Day 10 (± 2 days). Record the following information on the Dose Schedule Planner:
  1. The blast percentage from the patient's bone marrow assessment.
  2. The AUCATZYL bag serial number(s); number of bag type required for each dose; and the specified volume to administer via syringe (for the 10 × 10^6 dose, Blue Bag) transcribed from the Release for Infusion certificate.
3. The completion of the AUCATZYL Dose Schedule Planner will guide the treating physician on the number of bags required and preparation of AUCATZYL for the Day 1 and Day 10 (± 2 days) dose, see Figure 3.

Dose Preparation

Do NOT irradiate. Do NOT use a leukodepleting filter.

- Confirm the patient's identity with the patient identifiers on the Release for Infusion certificate. Contact Autolus Inc at 1-855-288-5227 if there are any discrepancies between the labels and the patient identifiers.
- Confirm tocilizumab and emergency equipment are available prior to infusion and during the recovery period.
- Coordinate the timing of AUCATZYL thaw and infusion. Confirm the infusion time in advance and adjust the start time of AUCATZYL thaw such that it will be available for infusion when the patient is ready and will be infused within 60 minutes of thaw.
- Complete the AUCATZYL Dose Schedule Planner, as described above to identify the dose required for Day 1 and Day 10 (± 2 days) administration, see Figure 3.
- Follow the completed AUCATZYL Dose Schedule Planner and refer to the patient batch specific Release for Infusion certificate to verify the bag(s) required for Day 1 or Day 10 (± 2 days) dosing, see Figure 3.

Transfer and Thawing

- Using the completed Dose Schedule Planner for guidance, transfer ONLY the cassette(s)/ infusion bag(s) required for the given dosing day from the onsite vapor phase liquid nitrogen storage to an appropriate transfer vessel (i.e., a vapor phase liquid nitrogen shipper, maintaining a temperature below minus 150°C) for transport to the bag thaw location.
- Transfer the required cassette(s) one by one, confirming the AUCATZYL bag serial numbers and patient identifiers on each infusion bag label, see Figure 2.
- Time out of the vapor phase liquid nitrogen environment should be kept to an absolute minimum to avoid premature product thaw (recommend not to exceed 90 seconds).
- If more than one infusion bag is required on a given dosing day, thaw each infusion bag one at a time; Do NOT remove subsequent bags from the vapor phase liquid nitrogen storage (below minus 150°C) until the infusion of the previous bag is complete.
- AUCATZYL must be continuously monitored during thawing process.
- Leave the AUCATZYL infusion bag in its overwrap, thaw at 37°C using a water bath or dry thaw method until there are no visible frozen clumps left in the infusion bag. Each bag should be gently massaged until the cells have just thawed. Thawing of each infusion bag takes between 2 and 8 minutes. Remove from water bath or thaw device immediately after thawing is complete. Carefully remove the infusion bag from the overwrap taking care to avoid damage to the bag and ports.
- Gently mix the contents of the bag to disperse clumps of cellular material and administer immediately to the patient.
- Do not re-freeze or refrigerate thawed product.

Figure 3: AUCATZYL Dosage and Schedule

Bone Marrow Blast > 20%
Day 1 |  | Day 10 (± 2 days)
10 × 10^6 Dose administered via syringe [Refer to Release for Infusion Certificate for the exact volume to be administered via syringe. Withdraw ONLY the volume.] |  | 100 × 10^6 Dose administered via bag infusion [The 100 × 10^6 (Orange Bag) and 300 × 10^6 (Red Bag) doses will be suspended in one or more infusion bags.] and 300 × 10^6 Dose administered via bag infusion
Bone Marrow Blast ≤ 20%
Day 1 |  | Day 10 (± 2 days)
100 × 10^6 Dose administered via bag infusion |  | 10 × 10^6 Dose administered via syringe and 300 × 10^6 Dose administered via bag infusion

2.4 Infusion Instructions

AUCATZYL is for autologous and intravenous use only.

The patient's identity must match the patient identifiers on the Release for Infusion certificate and infusion bag. Contact Autolus Inc at 1-855-288-5227 if there are any discrepancies between the labels and the patient identifiers.

Dose administration for 10 × 10^6 CD19 CAR-positive viable T cell Dose (Blue Bag)

Withdrawal of the 10 × 10^6 dose into the syringe should be carried as follows:

- Prepare and administer AUCATZYL using aseptic technique.
- Gently mix the contents of the bag to disperse clumps of cellular material.
- The volume to be administered for the 10 × 10^6 dose (Blue Bag) is specified on the Release for Infusion certificate.
- Use the smallest Luer-lock tip syringe necessary (1, 3, 5, or 10 mL) with a Luer-lock bag spike to draw up the volume as specified on the Release for Infusion certificate.
  - Do NOT use a leukodepleting filter.
  - Do NOT use the syringe to mix the cells, see Figure 4.

Figure 4: Syringe Infusion Guidance for the 10 × 10^6 Dose (Blue Bag)

Withdraw the volume from the 10 × 10^6 Dose (Blue Bag) specified on the Release for Infusion certificate using a syringe fitted with a bag spike.

Do not use the syringe to mix the cells

Confirm withdrawal of the exact volume specified on the Release for Infusion certificate for the 10 × 10^6 Dose (Blue Bag).

- Prime the tubing with normal saline prior to infusion.
- Once AUCATZYL has been drawn into the syringe, verify the volume and administer as an intravenous infusion as soon as possible as a slow push (approximately 0.5 mL/minute) through a central venous line (or large peripheral venous access line appropriate for blood products).
- Complete infusion at room temperature within 60 minutes post thaw and flush the tubing line with 60 mL of normal saline.
- Dispose of any unused portion of AUCATZYL (according to local biosafety guidelines).

Dose administration for 100 × 10^6 (Orange Bag) and/or 300 × 10^6 (Red Bag) CD19 CAR-positive viable T cells

Refer to the Release for Infusion certificate and Dose Schedule Planner for the following details:

- The volume and total CD19 CAR-positive viable T cell number contained in each infusion bag.
- The dose to be administered on the given dosing day and the number of bags required to deliver the specified CD19 CAR-positive viable T cell dose.
- If more than one bag is needed, thaw subsequent bags after the previous bag is fully administered.

1. Prime the tubing with normal saline prior to infusion.
2. Administer AUCATZYL via a gravity or peristaltic pump assisted IV infusion through a central venous line (or large peripheral venous access line appropriate for blood products).
  - Do NOT use a leukodepleting filter.
  - Aseptic techniques must be applied when performing a venepuncture, spiking the ports, and through the cell administration process.
  - Gently mix the contents of the bag during AUCATZYL infusion to disperse cell clumps.
3. Infuse the entire content of the AUCATZYL infusion bag at room temperature within 60 minutes post thaw (infusion rate within 0.1 to 27 mL/minute).
  - After the entire content of the infusion bag is infused, rinse the bag with 30 mL of normal saline, then flush the tubing line with 60 mL of normal saline.
  - Repeat steps 1 - 3 for any additional infusion bags required on the given dosing day. Do NOT initiate thaw of the next bag until infusion of the previous bag is complete.

AUCATZYL contains human blood cells that are genetically modified with replication-incompetent lentiviral vector. Follow universal precautions and local biosafety guidelines for handling and disposal of AUCATZYL to avoid potential transmission of infectious diseases.

Monitoring

- Monitor patients for signs and symptoms of CRS, neurologic toxicities/ICANS and other acute toxicities daily for at least 7 days following each infusion.
- Continue to monitor patients for at least 2 weeks following each infusion.
- Instruct patients to remain within proximity of a healthcare facility for at least 2 weeks following each infusion.
- Avoid driving for at least 2 weeks after each infusion.

3 DOSAGE FORMS AND STRENGTHS

AUCATZYL is a cell suspension for infusion.

AUCATZYL contains a total recommended dose of 410 × 10^6 CD19 CAR-positive viable T cells supplied in three to five infusion bags.

The infusion volume is variable and is calculated based on the concentration of CD19 CAR-positive viable T cells [see How Supplied/Storage and Handling (16)].

See the Release for Infusion certificate for actual cell counts. The Release for Infusion certificate and Dose Schedule Planner will be provided to the infusion site in the product shipper and via Autolus' Scheduling Portal.

4 CONTRAINDICATIONS

None.

5 WARNINGS AND PRECAUTIONS

5.1 Cytokine Release Syndrome

Cytokine Release Syndrome (CRS) occurred following treatment with AUCATZYL. CRS was reported in 75% (75/100) of patients including Grade 3 CRS in 3% of patients.

The median time to onset of CRS was 8 days (range: 1 to 23 days) with a median duration of 5 days (range: 1 to 21 days). Sixty-eight percent of patients (51/75) experienced CRS after the first infusion, but prior to the second infusion of AUCATZYL with a median time to onset of 6 days (range: 1 to 10 days). Among patients with CRS, the most common manifestations of CRS included fever (100%), hypotension (35%) and hypoxia (19%) [see Adverse Reactions (6)].

The primary treatment for CRS was tocilizumab (73%; 55/75), with patients also receiving corticosteroids (21%; 16/75).

Prior to administering AUCATZYL, ensure that healthcare providers have immediate access to medications and resuscitative equipment to manage CRS. During and following treatment with AUCATZYL, closely monitor patients for signs and symptoms of CRS daily for at least 7 days following each infusion. Continue to monitor patients for CRS for at least 2 weeks following each infusion with AUCATZYL [see Dosage and Administration (2.1)]. Counsel patients to seek immediate medical attention should signs or symptoms of CRS occur at any time. At the first sign of CRS, immediately evaluate the patient for hospitalization and institute treatment with supportive care based on severity and consider further management per current practice guidelines.

5.2 Neurologic Toxicities

Neurologic toxicities including Immune Effector Cell-associated Neurotoxicity Syndrome (ICANS), which were fatal or life-threatening, occurred following treatment with AUCATZYL. Neurologic toxicities were reported in 64% (64/100) of patients, including Grade ≥ 3 in 12% of patients.

The median time to onset of neurologic toxicities was 10 days (range: 1 to 246 days) with a median duration of 13 days (range: 1 to 904 days). Fifty-five percent of patients (35/64) experienced neurologic toxicities after the first infusion but prior to the second infusion of AUCATZYL with a median time to onset of 6 days (range: 1 to 11 days). Among patients with neurologic toxicities, the most common symptoms (> 5%) included ICANS (38%), headache (34%), encephalopathy (33%), dizziness (22%), tremor (13%), anxiety (9%), insomnia (9%), and delirium (8%) [see Adverse Reactions (6)].

Immune Effector Cell-associated Neurotoxicity Syndrome (ICANS)

ICANS events occurred in 24% (24/100) of patients, including Grade ≥ 3 in 7% (7/100) of patients. Of the 24 patients who experienced ICANS, 33% (8/24) experienced an onset after the first infusion, but prior to the second infusion of AUCATZYL.

The median time to onset for ICANS events after the first infusion was 8 days (range: 1 to 10 days) and 6.5 days (range: 2 to 22 days) after the second infusion, with a median duration of 8.5 days (range: 1 to 53 days).

Eighty-eight percent (21/24) of patients received treatment for ICANS. All treated patients received high-dose corticosteroids and 42% (10/24) of patients received anti-epileptics prophylactically. Prior to administering AUCATZYL, ensure that healthcare providers have immediate access to medications and resuscitative equipment to manage ICANS.

During and following AUCATZYL administration, closely monitor patients for signs and symptoms of Neurologic Toxicity/ICANS. Following treatment with AUCATZYL, monitor patients daily for at least 7 days. Continue to monitor patients for at least 2 weeks following treatment with AUCATZYL. Avoid driving for at least 2 weeks after each infusion.

Counsel patients to seek medical attention should signs or symptoms of neurologic toxicity/ ICANS occur. At the first sign of Neurologic Toxicity/ICANS, immediately evaluate patients for hospitalization and institute treatment with supportive care based on severity and consider further management per current practice guidelines [see Dosage and Administration (2.1)].

5.3 Prolonged Cytopenias

Patients may exhibit cytopenias including anemia, neutropenia, and thrombocytopenia for several weeks after treatment with lymphodepleting chemotherapy and AUCATZYL. In patients who were responders to AUCATZYL, Grade ≥ 3 cytopenias that persisted beyond Day 30 following AUCATZYL infusion were observed in 71% (29/41) of patients and included neutropenia (66%, 27/41) and thrombocytopenia (54%, 22/41). Grade 3 or higher cytopenias that persisted beyond Day 60 following AUCATZYL infusion was observed in 27% (11/41) of patients and included neutropenia (17%, 7/41) and thrombocytopenia (15%, 6/41) [see Adverse Reactions (6)]. Monitor blood counts after AUCATZYL infusion.

5.4 Infections

Severe, including life-threatening and fatal infections occurred in patients after AUCATZYL infusion. Non-COVID-19 infections of all grades occurred in 67% (67/100) of patients. Grade 3 or higher non-COVID-19 infections occurred in 41% (41/100) of patients [see Adverse Reactions (6)].

AUCATZYL should not be administered to patients with clinically significant active systemic infections. Monitor patients for signs and symptoms of infection before and after AUCATZYL infusion and treat appropriately [see Dosage and Administration (2.2,2.3)]. Administer prophylactic antimicrobials according to local guidelines.

Grade 3 or higher febrile neutropenia was observed in 26% (26/100) of patients after AUCATZYL infusion and may be concurrent with CRS. In the event of febrile neutropenia, evaluate for infection and manage according to treatment guidelines as medically indicated.

Viral reactivation, potentially severe or life-threatening, can occur in patients treated with drugs directed against B cells. There is no experience with manufacturing AUCATZYL for patients with a positive test for human immunodeficiency virus (HIV) or with active hepatitis B virus (HBV) or active hepatitis C virus (HCV). Perform screening for HBV, HCV and HIV in accordance with clinical guidelines before collection of cells for manufacturing.

5.5 Hypogammaglobulinemia

Hypogammaglobulinemia and B-cell aplasia can occur in patients after treatment with AUCATZYL. Hypogammaglobulinemia was reported in 10% (10/100) of patients treated with AUCATZYL including Grade 3 events in 2 patients (2%) [see Adverse Reactions (6)].

Immunoglobulin levels should be monitored after treatment with AUCATZYL and managed per institutional guidelines including infection precautions, antibiotic or antiviral prophylaxis and immunoglobulin replacement.

The safety of immunization with live viral vaccines during or following treatment with AUCATZYL has not been studied. Vaccination with live viral vaccines is not recommended for at least 6 weeks prior to the start of lymphodepleting chemotherapy treatment, during AUCATZYL treatment, and until immune recovery following treatment AUCATZYL.

5.6 Hemophagocytic Lymphohistiocytosis/Macrophage Activation Syndrome

Hemophagocytic Lymphohistiocytosis/Macrophage Activation Syndrome (HLH/MAS), including fatal and life-threatening reactions occurred after treatment with AUCATZYL. HLH/MAS was reported in 2% (2/100) of patients and included Grade 3 and Grade 4 events with a time of onset at Day 22 and Day 41, respectively. One patient experienced a concurrent ICANS events after AUCATZYL infusion and died due to sepsis with ongoing HLH/MAS that had not resolved [see Adverse Reactions (6)].

Administer treatment for HLH/MAS according to institutional standards.

5.7 Hypersensitivity Reactions

Serious hypersensitivity reactions, including anaphylaxis, may occur due to dimethyl sulfoxide (DMSO), an excipient used in AUCATZYL. Observe patients for hypersensitivity reactions during and after AUCATZYL infusion.

5.8 Secondary Malignancies

Patients treated with AUCATZYL may develop secondary malignancies. T cell malignancies have occurred following treatment of hematologic malignancies with BCMA- and CD19-directed genetically modified autologous T cell immunotherapies. Mature T cell malignancies, including CAR-positive tumors, may present as soon as weeks following infusion, and may include fatal outcomes [see Adverse Reactions (6)].

Monitor lifelong for secondary malignancies. In the event that a secondary malignancy occurs, contact Autolus Inc at 1-855-288-5227 for reporting and to obtain instructions on the collection of patient samples for testing.

6 ADVERSE REACTIONS

6.1 Clinical Trials Experience

Because clinical trials are conducted under widely varying conditions, adverse reaction rates observed in the clinical trials of a drug cannot be directly compared to rates in the clinical trials of another drug and may not reflect the rates observed in practice.

The safety of AUCATZYL was evaluated in the FELIX study in which 100 patients with relapsed or refractory B-cell acute lymphoblastic leukemia (B-ALL) received AUCATZYL at a median dose of 410 × 10^6 CD19 CAR-positive viable T cells (range: 10 to 480 × 10^6 CD19 CAR-positive viable T cells with 90% of patients receiving the recommended dose of 410 × 10^6 ± 25%) [see Clinical Studies (14)].

The most common serious adverse reactions of any Grade (incidence ≥ 2%) included infections-pathogen unspecified, febrile neutropenia, ICANS, CRS, fever, bacterial infectious disorders, encephalopathy, fungal infections, hemorrhage, respiratory failure, hypotension, ascites, HLH/MAS, thrombosis and hypoxia.

Nine patients (9%) experienced fatal adverse reactions which included infections (sepsis, pneumonia, peritonitis), ascites, pulmonary embolism, acute respiratory distress syndrome, HLH/MAS and ICANS. Of the 9 patients, five patients who died from infections had pre-existing and ongoing neutropenia prior to receiving bridging therapy, lymphodepletion chemotherapy treatment and/or AUCATZYL.

Table 3 summarizes the adverse reactions (excluding laboratory abnormalities) that occurred in at least 10% of patients. Table 4 presents the most common Grade 3 or 4 laboratory abnormalities, occurring in at least 10% of patients.

Table 3: Adverse Reactions Occurring in ≥ 10% of Patients in FELIX Study (N=100)
Adverse Reaction | Any Grade (%) | Grade 3 or Higher (%)
Blood and lymphatic system disorders
Febrile neutropenia | 26 | 26
Coagulopathy [Is a composite that includes multiple related terms.] | 10 | 6
Cardiac disorders
Tachycardia | 12 | 0
Gastrointestinal disorders
Nausea | 29 | 2
Diarrhea | 26 | 0
Vomiting | 18 | 0
Abdominal pain | 16 | 1
Constipation | 11 | 0
General disorders and administration site conditions
Fever | 29 | 1
Pain | 23 | 0
Fatigue | 22 | 3
Edema | 12 | 0
Chills | 11 | 0
Immune system disorders
Cytokine release syndrome | 75 | 3
Hypogammaglobulinemia | 10 | 2
Infections and infestations
Infections - pathogen unspecified | 44 | 31
Viral infections excluding COVID-19 | 16 | 1
COVID-19 | 18 | 6
Bacterial infections | 26 | 11
Fungal infections | 15 | 5
Investigations
Weight decreased | 11 | 2
Metabolism and nutrition disorders
Decreased appetite | 13 | 3
Musculoskeletal and connective tissue disorders
Musculoskeletal pain | 36 | 4
Nervous system disorders
Immune effector cell-associated neurotoxicity syndrome | 24 | 7
Headache | 22 | 0
Encephalopathy [Encephalopathy includes aphasia, cognitive disorder, confusional state, depressed level of consciousness, disturbance in attention, dysarthria, dysgraphia, encephalopathy, lethargy, memory impairment, mental status changes, posterior reversible encephalopathy syndrome, somnolence.] | 21 | 4
Dizziness | 14 | 0
Respiratory, thoracic and mediastinal disorders
Cough | 14 | 0
Skin and subcutaneous tissue disorders
Rash | 17 | 1
Vascular disorders
Hypotension | 23 | 4
Hemorrhage | 20 | 4

Other clinically important adverse reactions that occurred in less than 10% of patients treated with AUCATZYL include the following:

- Cardiac disorders: arrhythmia (5%), palpitations (2%), cardiac failure (1%).
- Endocrine disorders: adrenal insufficiency (2%).
- Eye disorders: visual impairment (2%).
- Gastrointestinal disorders: stomatitis (5%), ascites (4%).
- Immune system disorders: graft versus host disease (4%), HLH/MAS (2%).
- Injury, poisoning and procedural complications: infusion related reaction (2%).
- Nervous system and psychiatric disorders: tremor (8%), motor dysfunction (6%), delirium (5%), seizure (2%).
- Renal disorders: renal impairment (7%).
- Respiratory disorders: respiratory failure (8%), pleural effusion (4%).
- Skin and subcutaneous tissue disorders: skin ulcer (2%).
- Vascular disorders: thrombosis (5%).

Table 4: Grade 3 or 4 [Laboratory abnormalities graded using NCI Common Terminology Criteria for Adverse Events version 5.0.] Laboratory Abnormalities that Worsened from Baseline [Baseline laboratory values were assessed prior to lymphodepleting chemotherapy.] in ≥ 10% of Patients in FELIX Study (N=100)
Laboratory Abnormality | Grades 3 or 4 (%)
Lymphocytopenia | 90
Leukopenia | 87
Neutropenia | 72
Thrombocytopenia | 48
Anemia | 43
Hyperferritinemia | 13
Aspartate aminotransferase increased | 10

6.2 Postmarketing Experience

Because adverse events to marketed products are reported voluntarily from a population of uncertain size, it is not always possible to reliably estimate their frequency or establish a causal relationship to product exposure. The following adverse event has been identified during postmarketing use of BCMA- or CD19-directed genetically modified autologous T cell immunotherapies:

Neoplasms: T cell malignancies.

8 USE IN SPECIFIC POPULATIONS

8.1 Pregnancy

Risk Summary

There are limited available data with AUCATZYL use in pregnant women. In the FELIX study, one patient became pregnant 6 months following treatment with AUCATZYL. The patient had a premature delivery at 30 weeks of pregnancy.

No animal reproductive and developmental toxicity studies have been conducted with AUCATZYL to assess whether AUCATZYL can cause fetal harm when administered to a pregnant woman.

It is not known if AUCATZYL has the potential to be transferred to the fetus and cause fetal toxicity. Based on the mechanism of action of AUCATZYL, if the transduced cells cross the placenta, they may cause fetal toxicity, including B-cell lymphocytopenia and hypogammaglobinemia. Therefore, AUCATZYL is not recommended for women who are pregnant. Pregnancy after AUCATZYL infusion should be discussed with the treating physician.

In the U.S. general population, the estimated background risk of major birth defects is 2% to 4% and of miscarriage is 15% to 20% of clinically recognized pregnancies.

8.2 Lactation

Risk Summary

There is no information regarding the presence of AUCATZYL in human milk, the effect on the breastfed infant, and the effects on milk production. The developmental and health benefits of breastfeeding should be considered along with the mother's clinical need for AUCATZYL and any potential adverse effects on the breastfed infant from AUCATZYL or from the underlying maternal condition.

8.3 Females and Males of Reproductive Potential

Pregnancy Testing

Pregnancy status of females with reproductive potential should be verified. Sexually active females of reproductive potential should have a negative pregnancy test before starting treatment with AUCATZYL.

Contraception

See the prescribing information for fludarabine and cyclophosphamide for information on the need for effective contraception in patients who receive lymphodepleting chemotherapy treatment.

There are insufficient exposure data to provide a recommendation concerning duration of contraception following treatment with AUCATZYL.

Infertility

There are no data on the effect of AUCATZYL on fertility.

8.4 Pediatric Use

The safety and efficacy of AUCATZYL have not been established in pediatric patients.

8.5 Geriatric Use

Of the 100 patients treated with AUCATZYL, 20 (20%) were 65 years of age and over. No overall differences in safety or effectiveness were observed between these patients and younger patients.

10 OVERDOSAGE

In FELIX study (all cohorts N=127), occurrences of overdose were observed at the administration of the first dose in 4% (5/127) of patients. All 5 patients had bone marrow blasts > 20% and should have received a first dose of 10 × 10^6 CAR-positive viable T cells but instead received a higher dose between 68 and 103 × 10^6 CAR-positive viable T cells. CRS, ICANS and HLH, including severe events, were observed in patients who received overdose of AUCATZYL.

In the event of a suspected overdose, closely monitor patients for any adverse reactions and administer treatment according to institutional practice and treatment guidelines.

11 DESCRIPTION

AUCATZYL (obecabtagene autoleucel) is a CD19-directed genetically modified autologous Tcell immunotherapy comprised of the patient's T cells that are transduced with a lentiviral vector to express an anti-CD19 chimeric antigen receptor (CAR). The CAR is composed of a murine anti-CD19 single chain variable fragment (scFv) linked to 4-1BB and CD3-zeta co-stimulatory domains.

AUCATZYL is prepared from the patient's own peripheral blood mononuclear cells, which are collected via a standard leukapheresis procedure. The mononuclear cells are enriched for T cells, activated and transduced with a replication-incompetent lentiviral vector containing the CD19 CAR transgene. The transduced T cells are expanded in cell culture, washed, formulated into a suspension, and then cryopreserved. AUCATZYL is frozen in patient-specific infusion bag(s) and thawed prior to infusion [see Dosage and Administration (2.3), How Supplied/Storage and Handling (16)]. The product must pass a sterility test before it is released to the treatment center. The thawed product is a colorless to pale yellow, very opalescent suspension that is essentially free from visible foreign particles.

In addition to T cells, AUCATZYL also contains non-transduced autologous T cells and non-T cells. The formulation contains phosphate-buffered saline (PBS) human serum albumin (HSA), ethylenediaminetetraacetic acid (EDTA) and 7.5% DMSO.

12 CLINICAL PHARMACOLOGY

12.1 Mechanism of Action

AUCATZYL is a CD19-directed genetically modified autologous T cell immunotherapy consisting of the patient's own T cells expressing an anti-CD19 CAR. Engagement of anti-CD19 CAR-positive T cells with CD19 expressed on target cells, such as cancer cells and normal B cells, leads to activation of the anti-CD19 CAR-positive T cells and downstream signaling through the CD3-zeta domain. Proliferation and persistence by the anti-CD19 CAR-positive T cells following activation are enhanced by the presence of the 4-1BB co-stimulatory domain. This binding to CD19 results in anti-tumor activity and killing of CD19-expressing target cells.

12.2 Pharmacodynamics

Serum levels of cytokines such as IL-2, IL-5, IL-6, IL-7, IL-8, IL-10, IL-15, TNF-α, IFN-γ, and granulocyte-macrophage colony-stimulating factors were evaluated pre- and post-AUCATZYL infusion, over 3 months. Peak elevation of plasma cytokines was observed within the first month after infusion and levels returned to baseline by Month 3.

Due to the on-target effect of AUCATZYL, a period of B cell aplasia is expected. B cell aplasia was observed in 93.1% of patients at 3 months and 80.0% at 6 months.

12.3 Pharmacokinetics

The pharmacokinetics (PK) of AUCATZYL were assessed in 90 patients with relapsed or refractory CD19+ B-ALL receiving a median dose of 410 × 10^6 CD19 CAR-positive viable T cells (range: 10 to 480 × 10^6 CD19 CAR-positive viable T cells).

Following Day 1 infusion, levels of the AUCATZYL transgene in peripheral blood exhibited an initial rapid expansion. The median time of maximal expansion to peak (Tmax) occurred at Day 14 (range: Day 2-55), demonstrated by a geometric mean peak CAR T concentration (Cmax) of 115,193 copies/µg genomic DNA (gDNA; range: 129-600,000) and a geometric mean area under the curve between Days 0 and 28 (AUC0-28d) of 1,147,631 day*copies/μg DNA (range: 17,900-7,230,000 day*copies/μg DNA). A higher expansion was observed in patients with bone marrow blasts > 20% compared to patients with bone marrow blast ≤ 20%.

Table 5: Summary of Pharmacokinetics Parameters for Transgene Levels by ddPCR in Peripheral Blood by Dose Regimen Received
Parameter | Statistics | Bone Marrow Blast [Bone Marrow Blast > 20% = dosage regimen of 10 × 10^6 then 400 × 10^6 CD19 CAR-positive viable T cells.] > 20% (N=59) | Bone Marrow Blast [Bone Marrow Blast ≤ 20% = dosage regimen 100 × 10^6 then 310 × 10^6 CD19 CAR-positive viable T cells.] ≤ 20% (N=31) | Total (N=90)
Cmax (copies/µg DNA) | n | 59 | 31 | 90
Cmax (copies/µg DNA) | Geometric Mean | 146,314 | 73,074 | 115,193
Cmax (copies/µg DNA) | (Geo-CV%) | (294.4) | (186.9) | (267.0)
Cmax (copies/µg DNA) | Min–Max | 129–600,000 | 9290–589,000 | 129–600,000
Tmax (days) | n | 59 | 31 | 90
Tmax (days) | Median | 20 | 11 | 14
Tmax (days) | Min–Max | 6–55 | 2–28 | 2–55
AUC0-28d (day*copies/µg DNA) | n | 52 | 29 | 81
AUC0-28d (day*copies/µg DNA) | Geometric Mean | 1,521,310 | 692,307 | 1,147,631
AUC0-28d (day*copies/µg DNA) | (Geo-CV%) | (191.3) | (226.8) | (219.5)
AUC0-28d (day*copies/µg DNA) | Min–Max | 17,900–6,730,000 | 70,400–7,230,000 | 17,900–7,230,000
AUC0-28d=area under the concentration-time curve (exposure) from Day 0 to Day 28; Cmax = maximum serum concentration; ddPCR = droplet digital polymerase chain reaction; DNA = deoxyribonucleic acid; Geo-CV% = geometric mean coefficient of variation; Tmax = time to maximum concentration.

No substantial differences in AUCATZYL expansion were observed between responding (CR/CRi) and non-responding (non-CR/CRi) patients. Furthermore, 75.9% (22/29) of patients who had ongoing remission had ongoing CAR T persistency at the last laboratory assessment, with a maximum observed persistency of 36.5 months.

Patients who received a first split dose of 10 × 10^6 cells (> 20% blast) demonstrated a higher expansion of CAR T cells (Cmax and AUC0-28d) compared to patients who received a first split dose of 100 × 10^6 cells (≤ 20% blast). Persistency was not impacted by tumor burden.

Patients who experience CRS had 1.8-fold higher mean bone marrow blast percentage and higher CAR T cell expansion (5.0-fold higher Cmax and 6.8-fold higher AUC0-28d [geometric mean]) compared to patients without CRS. Patients who experience ICANS had 1.8-fold higher mean bone marrow blast percentage and higher CAR T cell expansion (3.3-fold higher Cmax and 2.9-fold higher AUC0-28d [geometric mean]) compared to patients without ICANS.

Specific populations

Sex did not have a significant impact on the PK of AUCATZYL (Cmax, AUC0-28d or persistency).

Hepatic and renal impairment studies of AUCATZYL were not conducted.

12.6 Immunogenicity

The humoral immunogenicity of AUCATZYL was measured using an assay for the detection of anti-drug antibodies against AUCATZYL. In the FELIX study, 8.7% (11/127) of patients tested positive for anti-CD19 CAR antibodies pre-infusion. Treatment induced anti-CD19 CAR antibodies were detected in 1.6% (2/127) of patients.

The cellular immunogenicity of AUCATZYL was measured using an assay for the detection of T cell responses, measured by the production of interferon gamma (IFNγ) to the full length anti-CD19 CAR. Four percent (3/75) of patients tested positive in the cellular immunogenicity readout (IFNγ) post infusion.

There was no identified clinically significant effect of humoral and cellular immunogenicity on pharmacokinetics, pharmacodynamics, safety, or effectiveness of AUCATZYL.

13 NONCLINICAL TOXICOLOGY

13.1 Carcinogenesis, Mutagenesis, Impairment of Fertility

No in vivo or in vitro carcinogenicity, mutagenicity or genotoxicity studies have been conducted with AUCATZYL. No studies have been conducted to evaluate the effects of AUCATZYL on fertility.

14 CLINICAL STUDIES

The efficacy of AUCATZYL was evaluated in an open-label, multi-center, single-arm study (FELIX study; NCT04404660). The study enrolled patients with relapsed or refractory B-cell acute lymphoblastic leukemia (ALL). Eligible patients were adults with refractory ALL, first relapse following a remission lasting ≤ 12 months, relapsed or refractory ALL after two or more prior lines of systemic therapy, or relapsed or refractory ALL at least greater than 3 months after allogeneic stem cell transplantation (SCT) and had disease burden of ≥ 5% blasts in bone marrow at screening. The study excluded patients with isolated extramedullary disease, active or serious infections requiring systemic antimicrobials, active graft versus host disease, history or presence of central nervous system (CNS) disorders. Treatment was administered in the in-patient setting and consisted of lymphodepleting chemotherapy (fludarabine 30 mg/m^2 IV daily for 4 days; cyclophosphamide 500 mg/m^2 IV daily for 2 days starting with first dose of fludarabine) followed by AUCATZYL as a split dose infusion with a total recommended dose of 410 × 10^6 CD19 CAR-positive viable T cells.

A total of 112 patients were enrolled and underwent leukapheresis; 18 (16%) of whom discontinued without receiving AUCATZYL infusion due to the following: death (n=11), adverse event (n=1), physician decision (n=1), and manufacturing failure (n=5). Among the remaining 94 patients who received at least one infusion of AUCATZYL, 65 patients had ≥ 5% blasts in the bone marrow after screening and prior to the start of the lymphodepletion therapy, and received a conforming product, qualifying them as efficacy-evaluable patients.

The population characteristics of efficacy-evaluable patients were as follows: median age was 51 years (range: 20 to 77 years) with 7 patients (11%) ≤ 25 years of age and 14 patients (22%) ≥ 65 years of age, 35 patients (54%) were female, 47 patients (72%) were White, 8 patients (12%) were Asian and 1 patient (2%) was Black or African American. Twenty-one patients (32%) were of Hispanic or Latino ethnicity.

At enrollment, 35 patients (54%) were refractory to the last prior line of therapy, and 32 patients (49%) relapsed to first-line therapy within 12 months. The median number of prior lines of therapy was 2 (range: 1 to 6). Thirty-five patients (54%) received either blinatumomab or inotuzumab ozogamicin and 10 patients (15%) received both blinatumomab and inotuzumab ozogamicin, 22 (34%) patients received prior SCT therapy, 17 (26%) patients had Ph+ ALL and 13 (20%) patients had extramedullary disease. Fifty-nine patients (91%) received bridging therapy between leukapheresis and lymphodepleting chemotherapy.

The median dose was 410 × 10^6 CD19 CAR-positive viable T cells (range: 10 to 418 × 10^6 CD19 CAR-positive viable T cells). Fifty-eight patients (89%) received the target dose of 410 × 10^6 CD19 CAR-positive viable T cells (± 25%). Five patients (8%) only received the first dose, primarily due to adverse events (5%). The median time from leukapheresis to product release was 20 days (range: 17 to 23 days) and the median time from leukapheresis to AUCATZYL infusion was 35 days (range: 26 to 74 days).

The major efficacy outcome measures were rate and duration of complete remission within 3 months after infusion. Additional outcome measures were rate and duration of overall complete remission which includes complete remission and complete remission with incomplete hematologic recovery, at any time. The efficacy results are summarized in Table 6 below.

Table 6: Efficacy Results for FELIX Study
Endpoint | Efficacy-Evaluable N=65 n (%) | All Leukapheresed N=112 n (%)
Complete Remission (within 3 months) rate
n (%) | 27 (42%) | 40 (36%)
[95% CI] | [29%, 54%] | (27%, 45%)
Duration (months), median [95% CI] | 14.1 [6.1, NR] | 14.1 (6.2, NR)
(Range in months) | (0.5+, 21.2) | (0.5+, 21.2)
Overall Complete Remission (At Anytime) rate [Rate of Overall Complete Remission "At Anytime" includes Complete Remission and Complete Remission with incomplete hematologic recovery "At Anytime".]
n (%) | 41 (63%) | 60 (54%)
[95% CI] | [50%, 75%] | [44%, 63%]
Duration (months), median [95% CI] | 14.1 [6.2, NR] | 14.1 [8.1, NR]
(Range in months) | (0.03+, 21.2) | (0.03+, 21.2)
CI=confidence interval; NR=not reached.

Among patients in the efficacy-evaluable population who achieved a best response of complete remission "At Anytime" (N=33; 51%), the median duration for remission was 14.1 months (95% confidence interval [CI]: 6.1, not reached [NR]). Among patients in the efficacy-evaluable population in whom best response was complete remission with incomplete hematologic recovery "At Anytime" (N=8; 12%), the median duration of remission was 10.5 months (95% CI: 1.8, NR).

15 REFERENCES

Lee DW et al (2019), ASTCT Consensus Grading for Cytokine Release Syndrome and Neurologic Toxicity Associated with Immune Effector Cells. Biol Blood Marrow Transplant. 2019 Apr; 25(4):625-638.

16 HOW SUPPLIED/STORAGE AND HANDLING

AUCATZYL 410 × 10^6 CD19 CAR-positive viable T cells NDC (83047-410-04) is supplied in three to five infusion bags (see below) containing a frozen suspension of genetically modified autologous T cells in PBS, HSA, EDTA and 7.5% DMSO.

Each infusion bag of AUCATZYL is individually packed within an overwrap and then enclosed within a metal cassette. AUCATZYL is shipped from the manufacturing facility to the cellular therapy laboratory associated with the infusion center in a cryogenic shipper charged with liquid nitrogen. A Release for Infusion certificate is provided to the infusion site in the shipper and via the Autolus Scheduling Portal with the product.

Infusion bag configurations | Color Code | Fill Volume Range (min – max) | NDC Number
10 × 10^6 CD19 CAR-positive viable T cells in one 50 mL infusion bag | Blue | 10 mL | 83047-010-10
100 × 10^6 CD19 CAR-positive viable T cells in one or more 50 mL infusion bags | Orange | 10 to 20 mL | 83047-100-10
100 × 10^6 CD19 CAR-positive viable T cells in one 250 mL infusion bag | Orange | 30 to 70 mL | 83047-100-30
300 × 10^6 CD19 CAR-positive viable T cells in one or more 250 mL infusion bags | Red | 30 to 70 mL | 83047-300-30

STORAGE AND HANDLING

- Match the identity of the patient with the patient identifiers on the infusion bag upon receipt [see Dosage and Administration (2.3)].
- Store AUCATZYL frozen in the vapor phase of liquid nitrogen (below minus 150°C) [see Dosage and Administration (Section 2.3)].
- Thaw AUCATZYL prior to infusion [see Dosage and Administration (2.3)].
- Do not re-freeze after thawing.
- Do not irradiate AUCATZYL, as this could lead to inactivation.

17 PATIENT COUNSELING INFORMATION

Advise the patient to read the FDA-approved patient labeling (Medication Guide).

Discuss the following with the patient:

- Inform patients that there is a risk of manufacturing failure (4.5% [5/112 in clinical studies]). Therefore, a second manufacturing of AUCATZYL may be attempted, after a second leukapheresis collection.
- Inform patients that additional therapy (other than lymphodepletion) may be necessary before AUCATZYL manufacturing is completed. This may increase the risk of adverse events during the pre-infusion period, which could delay or prevent the administration of AUCATZYL.
- Advise patients to seek immediate attention if any of the following occur:
  - Cytokine Release Syndrome: Inform patients that symptoms may include fever, hypotension and hypoxia [see Warnings and Precautions (5.1) and Adverse Reactions (6)].
  - Neurologic Toxicity/ICANS: Inform patients that symptoms may include ICANS, headache, dizziness, anxiety, insomnia, delirium, tremor, and encephalopathy [see Warnings and Precautions (5.2) and Adverse Reactions (6)].
  - Prolonged Cytopenias: Inform patients that symptoms may include neutropenia, anemia, thrombocytopenia, or bleeding [see Warnings and Precautions (5.3) and Adverse Reactions (6)].
  - Severe Infections: Inform patients that they may exhibit signs or symptoms associated with infection, and that past infections can be reactivated following treatment with AUCATZYL [see Warnings and Precautions (5.4) and Adverse Reactions (6)].
  - Secondary Malignancies: Secondary malignancies, including T cell malignancies, have occurred following treatment with BCMA- and CD19-directed genetically modified autologous T cell immunotherapies [see Boxed Warning, Warnings and Precautions (5.8), Adverse Reactions (6)].

Advise patients of the need to:

- Avoid driving for at least 2 weeks after infusion.
- Have periodic monitoring of blood counts.
- Contact Autolus Inc at 1-855-288-5227 if they are diagnosed with a secondary malignancy [see Warnings and Precautions (5.8)].

MEDICATION GUIDE
AUCATZYL® [pronounced aw-kat-zil]
(obecabtagene autoleucel)

Read this Medication Guide before you start your AUCATZYL treatment. The more you know about your treatment, the more active you can be in your care. Talk with your healthcare provider if you have questions about your health condition or treatment. Reading this Medication Guide does not take the place of talking with your healthcare provider about your treatment.

What is the most important information I should know about AUCATZYL?
AUCATZYL may cause side effects that are life-threatening and can lead to death. Call or see your healthcare provider or get emergency help right away if you get any of the following:

- Fever (100.4°F/38°C or higher)
- Severe nausea, vomiting, diarrhea
- Severe headache
- Dizziness or light-headedness
- Difficulty breathing
- Confusion
- Fast or irregular heartbeat
- Low blood pressure
- Chills/shivering
- Shaking or twitching (tremor)

It is important to tell your healthcare provider that you received AUCATZYL and to show them your AUCATZYL Patient Wallet Card. Your healthcare provider may give you other medicines to treat your side effects.

What is AUCATZYL?
AUCATZYL is a treatment for adults with acute lymphoblastic leukemia. It is used following disease progression while on or after other treatment. AUCATZYL is a medicine made from your own white blood cells, which have been changed (genetically modified) to recognize and attack your leukemic cells.

Before getting AUCATZYL, tell your healthcare provider about all of your medical problems, including if you have or have had:

- Neurologic problems (such as seizures, stroke, new or worsening memory loss)
- Lung or breathing problems
- Heart problems
- A recent or active infection
- Past infections which can be reactivated following treatment with AUCATZYL
- Pregnancy, you think you may be pregnant, or plan to become pregnant
- Breastfeeding

Tell your healthcare provider about all the medication you take, including prescription and over-the-counter medicines, vitamins, dietary supplements, and herbal supplements.

How will I receive AUCATZYL?

- AUCATZYL is made from your own white blood cells, so your blood will be collected by a process called "leukapheresis" (loo-kah-fur-ee-sis), which will concentrate your white blood cells.

Step 1:

- Your blood cells will be sent to a manufacturing center to make your AUCATZYL.
- While waiting for AUCATZYL to be made, you may get other medicines to stabilize your cancer. This is so that your acute lymphoblastic leukemia does not get worse.
- Within 7 days before you start treatment, a sample of your cells will be taken to confirm your disease burden, this will determine which infusion dose you are given first.
- Your infusion dose will be tailored to the burden of your disease. This will be provided as two separate infusions.

Step 2:

- Before you receive AUCATZYL, your healthcare provider will give you chemotherapy for a few days to make room in the bone marrow.
- When your AUCATZYL is ready, your healthcare provider will give it to you through a catheter (tube) placed into your vein (intravenous infusion).
- After you receive your AUCATZYL first infusion you will receive your second infusion 10 days (± 2 days) later.
- 30 minutes before you are given AUCATZYL, you may be given medicines for fever (such as acetaminophen).

Step 3:

- After AUCATZYL infusion, you will be monitored daily for at least 7 days after the infusion so that your healthcare team can closely monitor your recovery.
- You should plan to stay close to a healthcare facility for at least 2 weeks after getting AUCATZYL. Your healthcare provider will help you with any side effects that may occur.
- You may be hospitalized for side effects. Your healthcare provider will determine when you can go home.
- Your healthcare provider will want to do blood tests to follow your progress. It is important that you do have your blood tested. If you miss an appointment, call your healthcare provider as soon as possible to reschedule.

What should I avoid after receiving AUCATZYL?

- Avoid driving for at least 2 weeks after you get AUCATZYL.
- Do not donate blood, organs, tissues, or cells for transplantation.

What are the possible side effects of AUCATZYL?
The most common side effects of AUCATZYL include:

- Fever (100.4°F/38°C or higher)
- Nausea
- Diarrhea
- Infections
- Headache
- Muscle or joint pain
- Fatigue or feeling very tired
- Low blood pressure (dizziness or light-headedness, headache, fatigue, short of breath)
- Fast irregular heartbeat
- Confusion
- Difficulty speaking or slurred speech
- Low white blood cells (can occur with a fever)
- Bleeding

AUCATZYL may increase your risk of getting cancers including certain types of blood cancers. Your healthcare provider should monitor you for this.
These are not all the side effects of AUCATZYL. Call your healthcare provider about any side effects that concern you. You may report side effects to FDA at 1-800-FDA-1088.

General information about the safe and effective use of AUCATZYL.
Medicines are sometimes prescribed for purposes other than those listed in a Medication Guide.
If you would like more information about AUCATZYL, talk with your healthcare provider. You can ask your healthcare provider for information about AUCATZYL that is written for health professionals. You can get additional information by contacting Autolus Inc at 1-855-288-5227 or at www.AUCATZYL.com

What are the ingredients in AUCATZYL?
Active ingredients: obecabtagene autoleucel
Inactive ingredients: albumin (human); DMSO

Manufactured by: Autolus Limited, Marshgate, Stevenage, SG1 1FR, United Kingdom.
Manufactured for: Autolus Inc., Gaithersburg, MD, 20877
US License No 2339
AUCATZYL is a registered trademark of Autolus Limited.
© 2024 Autolus Limited. All Rights Reserved.

This Medication Guide has been approved by the U.S. Food and Drug Administration.
Issued: 08/2025

PRINCIPAL DISPLAY PANEL - 10 mL Infusion Bag Label - 10 x 10

10x10^6 bag configuration

EXTRACT SPECIFIED VOLUME VIA SYRINGE

obecabtagene autoleucel

AUCATZYL®

FOR AUTOLOGOUS & INTRAVENOUS USE ONLY.

Dosage: See prescribing information and release for
infusion certificate. Discard unused portion.

Contains: Up to 100x10^6 CD19 CAR-positive viable
T cells in 10mL suspension containing 7.5% DMSO USP.

DO NOT USE A
LEUKODEPLETING FILTER
OR IRRADIATE.

Storage: Ship and store
in vapor phase of liquid
nitrogen ≤ -150°C.

Not evaluated for infectious substances.

Rx Only
US License 2339
A1001-01

Autolus

Mfd by: Autolus Ltd, Stevenage, SG1 1FR, UK
Mfd for: Autolus Inc., Gaithersburg, MD, 20877
Phone: 1-855-288-5227

PRINCIPAL DISPLAY PANEL - 10 mL to 20 mL Infusion Bag Label - 100 x 10

100x10^6 bag configuration

obecabtagene autoleucel

AUCATZYL®

FOR AUTOLOGOUS & INTRAVENOUS USE ONLY.

Dosage: See prescribing information and the release for
infusion certificate.

Contains: 100x10^6 CD19 CAR-positive viable T cells in
10mL to 20mL suspension containing 7.5% DMSO USP.

Dose may be suspended in 1 or more infusion bag(s).

DO NOT USE A
LEUKODEPLETING FILTER
OR IRRADIATE.

Storage: Ship and store
in vapor phase of liquid
nitrogen ≤ -150°C.

Not evaluated for infectious substances.

Rx Only
US License 2339
D1001-01

Autolus

Mfd by: Autolus Ltd, Stevenage, SG1 1FR, UK
Mfd for: Autolus Inc., Gaithersburg, MD, 20877
Phone: 1-855-288-5227

PRINCIPAL DISPLAY PANEL - 30 mL to 70 mL Infusion Bag Label - 100 x 10

100x10^6 bag configuration

obecabtagene autoleucel

AUCATZYL®

FOR AUTOLOGOUS & INTRAVENOUS USE ONLY.

Dosage: See prescribing information and the release for
infusion certificate.

Contains: 100x10^6 CD19 CAR-positive viable T cells in
30mL to 70mL suspension containing 7.5% DMSO USP.

DO NOT USE A
LEUKODEPLETING FILTER
OR IRRADIATE.

Storage: Ship and store
in vapor phase of liquid
nitrogen ≤ -150°C.

Not evaluated for infectious substances.

Rx Only
US License 2339
B1001-01

Autolus

Mfd by: Autolus Ltd, Stevenage, SG1 1FR, UK
Mfd for: Autolus Inc., Gaithersburg, MD, 20877
Phone: 1-855-288-5227

PRINCIPAL DISPLAY PANEL - 30 mL to 70 mL Infusion Bag Label - 300 x 10

300x10^6 bag configuration

obecabtagene autoleucel

AUCATZYL®

FOR AUTOLOGOUS & INTRAVENOUS USE ONLY.

Dosage: See prescribing information and the release for
infusion certificate.

Contains: 300x10^6 CD19 CAR-positive viable T cells in
30mL to 70mL suspension containing 7.5% DMSO USP.

Dose may be suspended in 1 or more infusion bag(s).

DO NOT USE A
LEUKODEPLETING FILTER
OR IRRADIATE.

Storage: Ship and store
in vapor phase of liquid
nitrogen ≤ -150°C.

Not evaluated for infectious substances.

Rx Only
US License 2339
C1001-01

Autolus

Mfd by: Autolus Ltd, Stevenage, SG1 1FR, UK
Mfd for: Autolus Inc., Gaithersburg, MD, 20877
Phone: 1-855-288-5227

PRINCIPAL DISPLAY PANEL - Patient Information Label

obecabtagene autoleucel
AUCATZYL®

VERIFY
PATIENT
ID

Aph ID:
Lot/COI ID:
Patient Hospital ID:
First Name M.I.:
Last Name:
DOB: DD-MMM-YYYY
Expiry: DD-MMM-YYYY
S/N:

A

P1001-01

PRINCIPAL DISPLAY PANEL - Kit Label

obecabtagene autoleucel
AUCATZYL®

FOR AUTOLOGOUS & INTRAVENOUS USE ONLY.

Dose: 410 x 10^6 CD19 CAR-positive viable T cells

Dosage: See prescribing information and the release for infusion certificate.

Contains: AUCATZYL is a frozen cell suspension containing 7.5% DMSO.
Supplied in three to five infusion bag(s) in one or two packs.

Ship and store in vapor phase of liquid nitrogen ≤ -150°C.

Upon receipt, immediately transfer to a vapor phase liquid nitrogen
environment (≤ -150°C). Do not refreeze.

DO NOT USE A LEUKODEPLETING FILTER OR IRRADIATE.

Rx Only

KIT NDC: 83047-410-04

Lot/COI ID :

Aph ID :

Expiry : DD-MMM-YYYY

1/X Pack

Autolus

M3001-01

Manufactured by Autolus Ltd, Stevenage, SG1 1FR, UK
Manufactured for Autolus Inc., Gaithersburg, MD, 20877
Phone: 1-855-288-5227
US License 2339